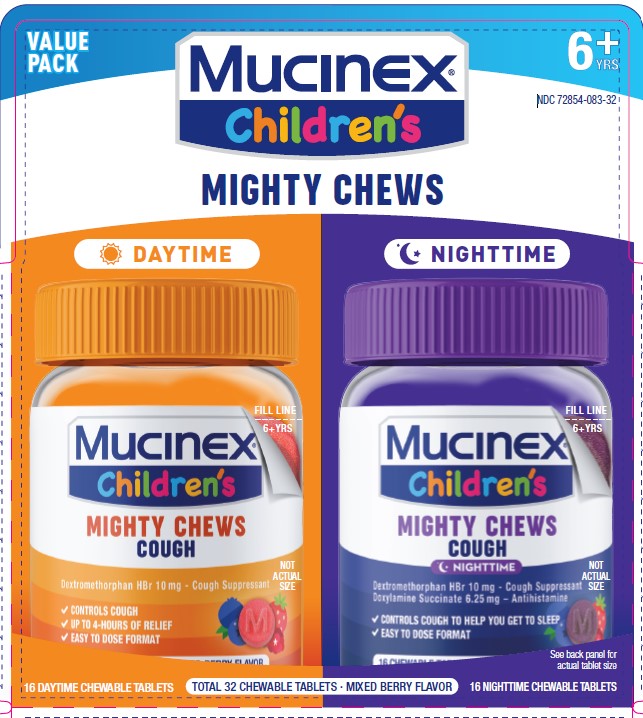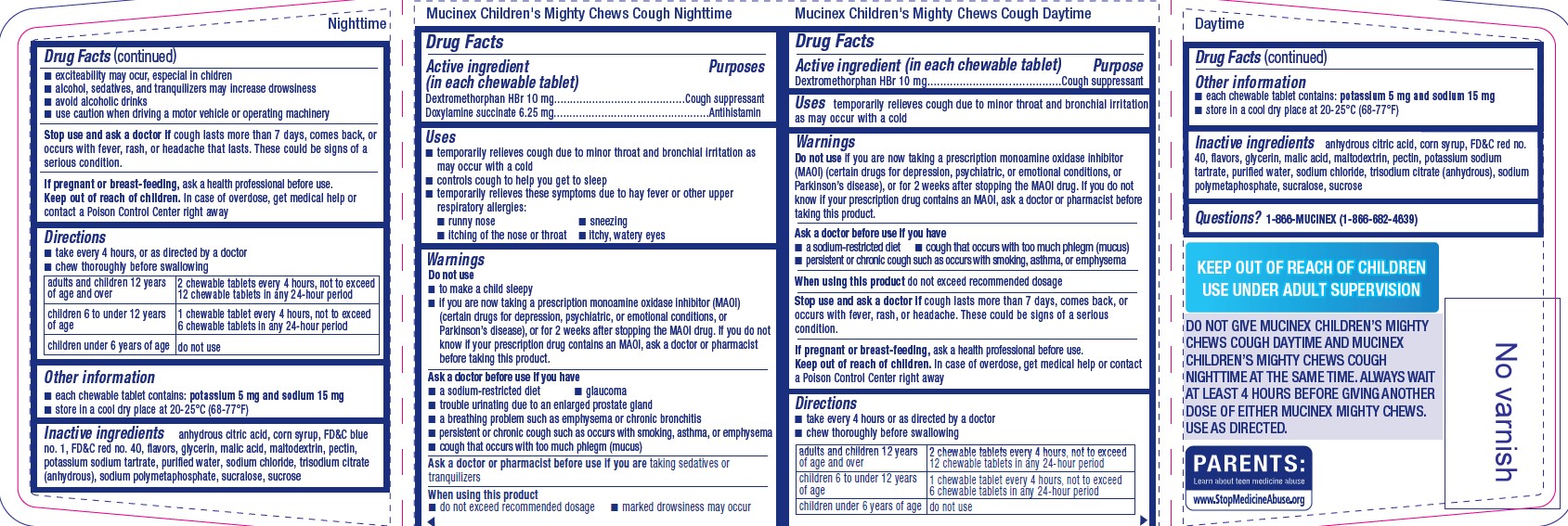 DRUG LABEL: Mucinex Childrens Mighty Chews Cough Daytime and Nighttime Combo Pack
NDC: 72854-083 | Form: KIT | Route: ORAL
Manufacturer: RB Health (US) LLC
Category: otc | Type: HUMAN OTC DRUG LABEL
Date: 20241119

ACTIVE INGREDIENTS: DEXTROMETHORPHAN HYDROBROMIDE 10 mg/1 1; DOXYLAMINE SUCCINATE 6.25 mg/1 1; DEXTROMETHORPHAN HYDROBROMIDE 10 mg/1 1
INACTIVE INGREDIENTS: ANHYDROUS CITRIC ACID; SODIUM CHLORIDE; SUCROSE; SODIUM POLYMETAPHOSPHATE; WATER; ANHYDROUS TRISODIUM CITRATE; SUCRALOSE; FD&C RED NO. 40; MALTODEXTRIN; POTASSIUM SODIUM TARTRATE; PECTIN; CORN SYRUP; GLYCERIN; MALIC ACID; FD&C RED NO. 40; PECTIN; SODIUM POLYMETAPHOSPHATE; SUCRALOSE; ANHYDROUS CITRIC ACID; WATER; POTASSIUM SODIUM TARTRATE; ANHYDROUS TRISODIUM CITRATE; SODIUM CHLORIDE; SUCROSE; CORN SYRUP; GLYCERIN; MALTODEXTRIN; FD&C BLUE NO. 1; MALIC ACID

Mucinex Childrens Mighty Chews Cough Daytime and Nighttime Combo Pack

ACTIVE INGREDIENT

Mucinex Children's Mighty Chews Cough Daytime:

Active ingredient (in each chewable tablet)
Dextromethorphan HBr 10 mg.

Mucinex Children's Mighty Chews Cough Nighttime:

Active ingredient (in each chewable tablet)
Dextromethorphan HBr 10 mg
Doxylamine succinate 6.25 mg

PURPOSE

Dextromethorphan HBr 10 mg.......................... ...............Cough suppressant
Doxylamine succinate 6.25 mg.................................................Antihistamin

Uses

Mucinex Children's Mighty Chews Cough Daytime:

Uses temporarily relieves cough due to minor throat and bronchial irritation
as may occur with a cold

Mucinex Children's Mighty Chews Cough Nighttime:

Uses
■ temporarily relieves cough due to minor throat and bronchial irritation as
may occur with a cold
■ controls cough to help you get to sleep
■ temporarily relieves these symptoms due to hay fever or other upper
respiratory allergies:
■ runny nose

■ sneezing
■ itching of the nose or throat

■ itchy, watery eyes

WARNINGS

Mucinex Children's Mighty Chews Cough Daytime:

Warnings
Do not use if you are now taking a prescription monoamine oxidase inhibitor
(MAOI) (certain drugs for depression, psychiatric, or emotional conditions, or
Parkinson’s disease), or for 2 weeks after stopping the MAOI drug. If you do not
know if your prescription drug contains an MAOI, ask a doctor or pharmacist before
taking this product.

Ask a doctor before use if you have
■ a sodium-restricted diet

■ cough that occurs with too much phlegm (mucus)
■ persistent or chronic cough such as occurs with smoking, asthma, or emphysema
When using this product do not exceed recommended dosage

Stop use and ask a doctor if cough lasts more than 7 days, comes back, or
occurs with fever, rash, or headache. These could be signs of a serious
condition.

Mucinex Children's Mighty Chews Cough Nighttime:

Warnings
Do not use
■ to make a child sleepy
■ if you are now taking a prescription monoamine oxidase inhibitor (MAOI)
(certain drugs for depression, psychiatric, or emotional conditions, or
Parkinson’s disease), or for 2 weeks after stopping the MAOI drug. If you do not
know if your prescription drug contains an MAOI, ask a doctor or pharmacist
before taking this product.

Ask a doctor before use if you have
■ a sodium-restricted diet

■ glaucoma
■ trouble urinating due to an enlarged prostate gland
■ a breathing problem such as emphysema or chronic bronchitis
■ persistent or chronic cough such as occurs with smoking, asthma, or emphysema
■ cough that occurs with too much phlegm (mucus)

Ask a doctor or pharmacist before use if you are taking sedatives or
tranquilizers

When using this product
■ do not exceed recommended dosage

■ marked drowsiness may occur

■ exciteability may ocur, especial in chidren
■ alcohol, sedatives, and tranquilizers may increase drowsiness
■ avoid alcoholic drinks
■ use caution when driving a motor vehicle or operating machinery

Stop use and ask a doctor if cough lasts more than 7 days, comes back, or
occurs with fever, rash, or headache that lasts. These could be signs of a
serious condition.

KEEP OUT OF REACH OF CHILDREN

If pregnant or breast-feeding, ask a health professional before use

.
Keep out of reach of children. In case of overdose, get medical help or
contact a Poison Control Center right away

Directions

Mucinex Children's Mighty Chews Cough Daytime+Mucinex Children's Mighty Chews Cough Nighttime::

■ take every 4 hours or as directed by a doctor
■ chew thoroughly before swallowing

adults and children 12 years of age and over | 2 chewable tablets every 4 hours, not to exceed 12 chewable tablets in any 24-hour period
children 6 to under 12 years of age | 1 chewable tablet every 4 hours, not to exceed 6 chewable tablets in any 24-hour period
children under 6 years of age | do not use

Other information
■ each chewable tablet contains: potassium 5 mg and sodium 15 mg
■ store in a cool dry place at 20-25°C (68-77°F)

INACTIVE INGREDIENT

Mucinex Children's Mighty Chews Cough Daytime:

Inactive ingredients anhydrous citric acid, corn syrup, FD&C red no.
40, flavors, glycerin, malic acid, maltodextrin, pectin, potassium sodium
tartrate, purified water, sodium chloride, trisodium citrate (anhydrous), sodium
polymetaphosphate, sucralose, sucrose

Mucinex Children's Mighty Chews Cough Nighttime:

Inactive ingredients anhydrous citric acid, corn syrup, FD&C blue
no. 1, FD&C red no. 40, flavors, glycerin, malic acid, maltodextrin, pectin,
potassium sodium tartrate, purified water, sodium chloride, trisodium citrate
(anhydrous), sodium polymetaphosphate, sucralose, sucrose

Questions? 1-866-MUCINEX (1-866-682-4639)

PACKAGE LABEL

NDC 72854-083-32

DAY & NIGHT MIGHTY CHEWS COUGH

Mucinex®Childrens
Dextromethorphan HBr – Cough Suppressant

Doxylamine succinate - Antihistamin

16 Chewable Tablets each